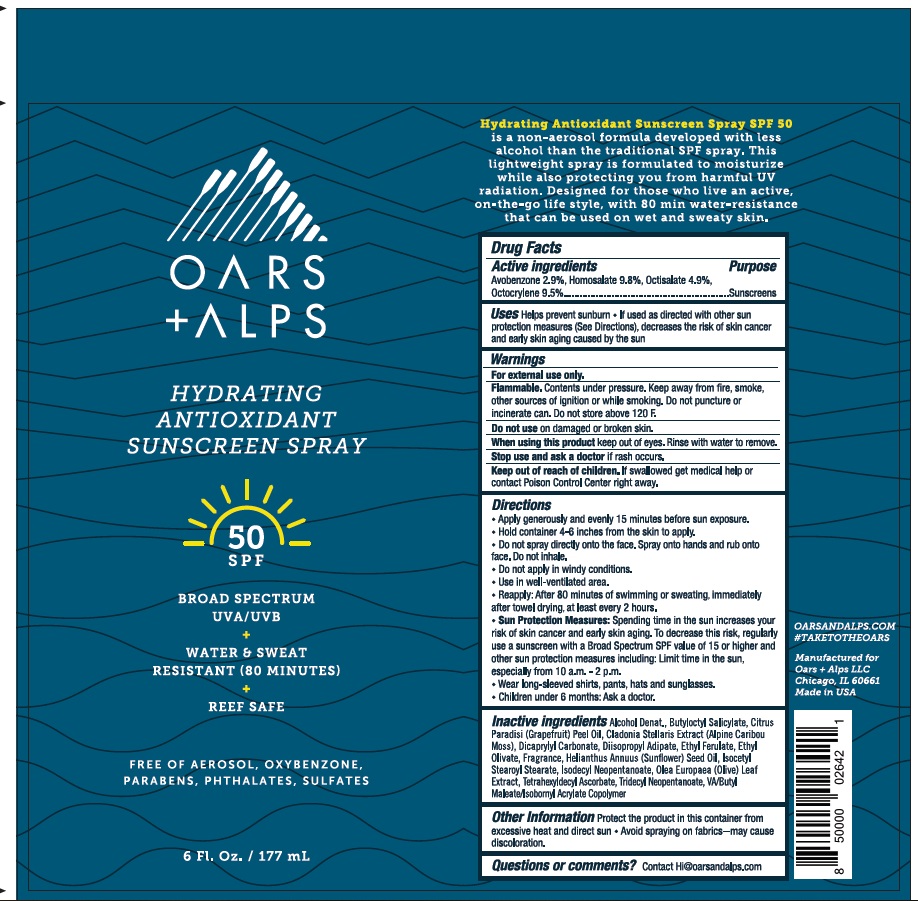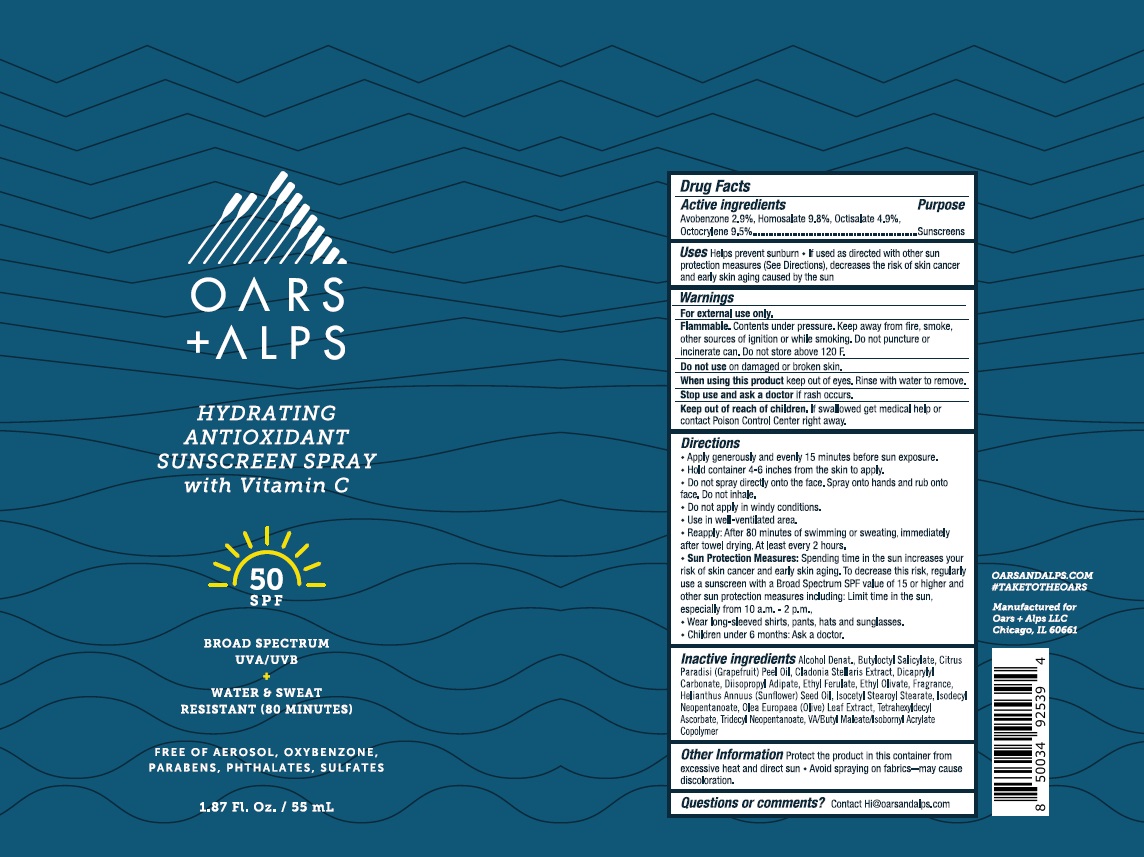 DRUG LABEL: Oars and Alps SPF 50 Hydrating Antioxidant SunscreenSpray
NDC: 83046-360 | Form: SPRAY
Manufacturer: Oars and Alps LLC
Category: otc | Type: HUMAN OTC DRUG LABEL
Date: 20241220

ACTIVE INGREDIENTS: AVOBENZONE 2.9 g/100 mL; HOMOSALATE 9.8 g/100 mL; OCTISALATE 4.9 g/100 mL; OCTOCRYLENE 9.5 g/100 mL
INACTIVE INGREDIENTS: BUTYLOCTYL SALICYLATE; ETHYL OLIVATE; ISOCETYL STEAROYL STEARATE; ISODECYL NEOPENTANOATE; OLEA EUROPAEA LEAF; TETRAHEXYLDECYL ASCORBATE; TRIDECYL NEOPENTANOATE; ISOBORNYL ACRYLATE; VINYL ACETATE; ALCOHOL; ETHYL FERULATE; GRAPEFRUIT OIL; CLADONIA RANGIFERINA WHOLE; DICAPRYLYL CARBONATE; DIISOPROPYL ADIPATE; SUNFLOWER OIL; DIBUTYL MALEATE

Oars & Alps SPF 50 Hydrating Antioxidant Sunscreen Spray

ACTIVE INGREDIENT

Avobenzone - 2.9%
Homosalate - 9.8%
Octisalate - 4.9%
Octocrylene - 9.5%

PURPOSE

Sunscreen

Uses

• Helps prevent sunburn

• If used as directed with other sun protection measures (see Directions), decreases the risk of skin cancer and early skin aging caused by the sun.

WARNINGS

- For external use only.
- Flammable. Contents under pressure. Keep away from fire, smoke, other sources of ignition or while smoking. Do not puncture of incinerate can. Do not store above 120 F.
- Do not use on damaged or broken skin.
- When using this product keep out of eyes. Rinse with water to remove.
- Stop use and ask a doctor if rash occurs.

Keep out of reach of children. If swallowed, get medical help or contact a Poison Control Center right away.

Directions

- Apply generously and evenly 15 minutes before sun exposure
- Hold container 4-6 inches from the skin to apply
- Do not spray directly onto the face. Spray onto hands and rub onto face. Do not inhale.
- Do not apply in windy conditions.
- Use in well ventilated area.
- Reapply: After 80 minutes of swimming or sweating, immedately after towl drying, at least every 2 hours.
- Sun Protection Measures: Spending time in the sun increases your risk of skin cancer and early skin aging. To decrease this risk, regularly use a sunscreen with a Broad Spectrum SPF value of 15 or higher and other sun protection measures including: • Limit time in the sun especially from 10 a.m. – 2 p.m. • Wear long-sleeved shirts, pants, hats, and sunglasses.
- Children under six months: Ask a doctor.

INACTIVE INGREDIENT

Alcohol Denat., Butyloctyl Salicylate, Citrus Paradisi (Grapefruit) Peel Oil, Cladonia Stellaris Extract, Dicaprylyl Carbonate, Diisopropyl Adipate, Ethyl Ferulate, Ethyl Olivate, Fragrance, Helianthus Annuus (Sunflower) Seed Oil, Isocetyl Stearoyl Stearate, Isodecyl Neopentanoate, Olea Europaea (Olive) Leaf Extract, Tetrahexyldecyl Ascorbate, Tridecyl Neopentanoate, VA/Butyl Maleate/Isobornyl Acrylate Copolymer

OTHER SAFETY INFORMATION

- Protect the product in this container from excessive heat and direct sun
- Avoid spraying on facbrics - may cause discoloration

QUESTIONS

Contact Hi@oarsandalps.com